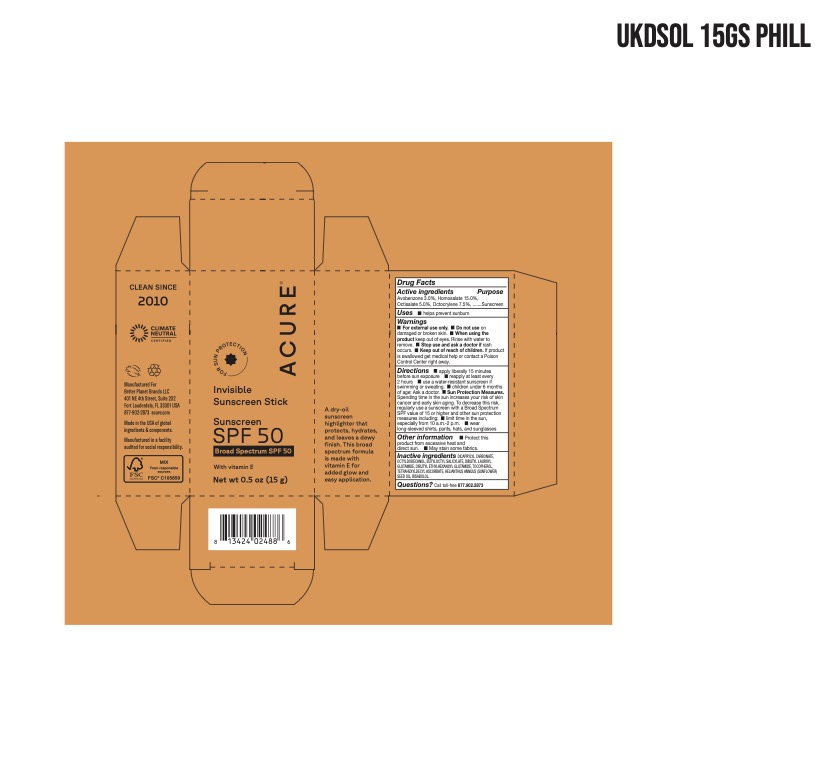 DRUG LABEL: Invisible Sunscreen Stick SPF 50
NDC: 54136-350 | Form: STICK
Manufacturer: Better Planet Brands LLC
Category: otc | Type: HUMAN OTC DRUG LABEL
Date: 20251203

ACTIVE INGREDIENTS: HOMOSALATE 15 g/100 g; OCTOCRYLENE 7.5 g/100 g; AVOBENZONE 3 g/100 g; OCTISALATE 5 g/100 g
INACTIVE INGREDIENTS: DICAPRYLYL CARBONATE; LEVOMENOL; BUTYLOCTYL SALICYLATE; DIBUTYL ETHYLHEXANOYL GLUTAMIDE; TETRAHEXYLDECYL ASCORBATE; DIBUTYL LAUROYL GLUTAMIDE; OCTYLDODECANOL; .ALPHA.-TOCOPHEROL ACETATE, D-; SUNFLOWER OIL

Invisible Sunscreen Stick SPF 50

Active ingredients

Avobenzone 3.0%
Homosalate 15.0%
Octisalate 5.0%
Octocrylene 7.5%

Purpose

Sunscreen

Uses

• helps prevent sunburn

Warnings

• For external use only.

Do not use on damaged or broken skin.

WHEN USING

When using the product * keep out of eyes. Rinse with water to remove.

Stop use and ask a doctor if rash occurs.

Keep out of reach of children. If product is swallowed get medical help or contact a Poison Control Center right away.

Directions

• apply liberally 15 minutes before sun exposure reapply at least every 2 hours • use a water-resistant sunscreen if swimming or sweating. • Sun Protection

Measures. Spending time in the sun increases your risk of skin cancer and early skin aging. To decrease this risk, regularly use a sunscreen with a Broad Spectrum SPF value of 15 or higher and other sun protection measures including: • limit time in the sun, especially from 10 a.m.-2 p.m.

• wear

long-sleeved shirts, pants, hats, and sunglasses

Other information

Protect this product from excessive heat and direct sun. • May stain some fabrics.

Inactive Ingredients

DICAPRYLYL CARBONATE, OCTYLDODECANOL, BUTYLOCTYL SALICYLATE, DIBUTYL LAUROYL

GLUTAMIDE, DIBUTYL ETHYLHEXANOYL GLUTAMIDE, TOCOPHEROL, TETRAHEXYLDECYL ASCORBATE, HELIANTHUS ANNUUS (SUNFLOWER) SEED OIL, BISABOLOL

Questions?

Call toll-free 877.902.2873